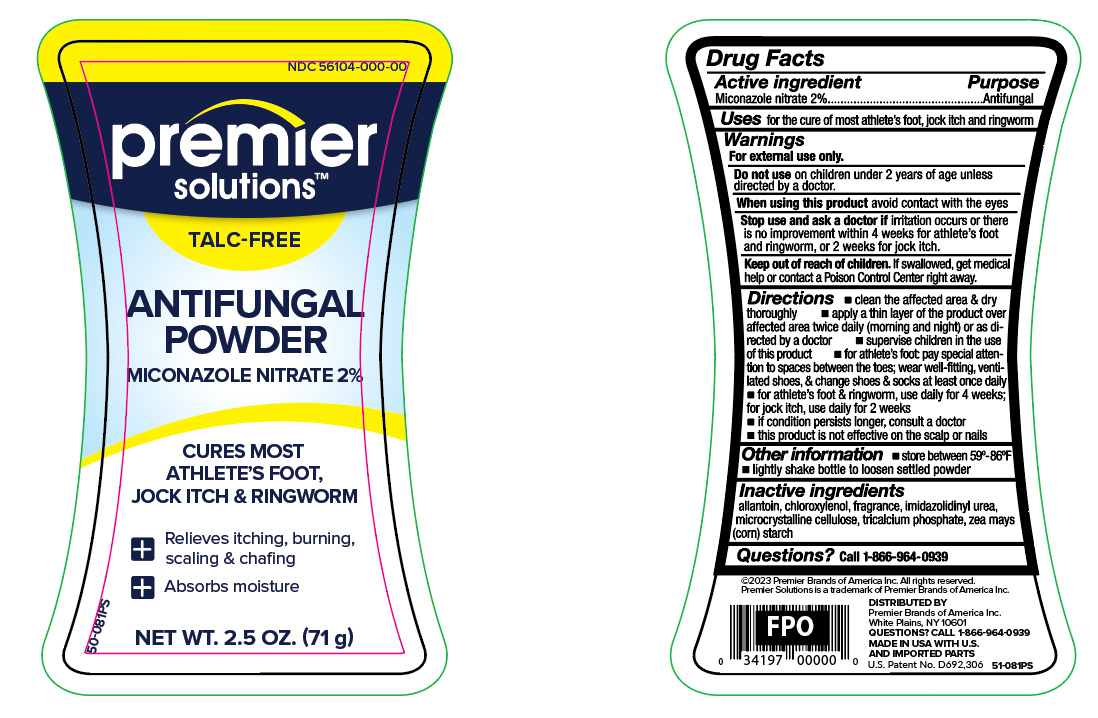 DRUG LABEL: Anti- Fungal Miconazole Nitrate
NDC: 56104-253 | Form: POWDER
Manufacturer: Premier Brands of America Inc.
Category: otc | Type: HUMAN OTC DRUG LABEL
Date: 20250806

ACTIVE INGREDIENTS: MICONAZOLE NITRATE 1.42 g/71 g
INACTIVE INGREDIENTS: ALLANTOIN; CHLOROXYLENOL; IMIDUREA; MICROCRYSTALLINE CELLULOSE; TRICALCIUM PHOSPHATE; ZEA MAYS SUBSP. MAYS WHOLE

Premier Solutions MiconazoleAF Powder - Talc Free

Active ingredient

Miconazole nitrate 2%

Purpose

Antifungal

Uses

for the cure of most athlete's foot, jock itch and ringworm

Warnings

For external use only.

Do not use

on children 2 years of age unless directed by a doctor.

When using this product

avoid contact with the eyes.

Stop and ask a doctor if

irritation occurs or there is no improvement within 4 weeks for athlete's foot and ringworm, or 2 weeks for jock itch.

Keep out of reach of children.

If swallowed, get medical help or contact a Poison Control Center right away.

Directions

- clean the affected area & dry thoroughly
- apply a thin layer of product over affected area twice daily (morning and night) or as directed by a doctor
- supervise children in the use of this product
- for athlete's foot: pay special attention to spaces between the toes; wear well-fitting, ventilated shoes, and change shoes and socks at least once daily
- for athlete's foot and ringworm, use daily for 4 weeks; for jock itch, use daily for 2 weeks
- if conditions persist longer, consult a doctor
- this product is not effective on the scalp or nails

Other information

- store between 59º - 86ºF
- lightly shake bottle to loosen settled powder

Inactive ingredient

allantoin, chloroxylenol, fragrance, imidazolidinyl urea, microcrystalline cellulose, tricalicum phosphate, zea mays (corn) starch

Questions?

call 1-866-964-0939

Principal Display Panel

CORE VALUES

Absorbs Moisture

Miconazorb AF

ANTI-FUNGAL POWDER

Miconazole Nitrate 2%

Cures Most:

- Athlete's foot
- Jock itch
- Ringworm

Relieves itching, burning, scaling and chafing

Talc-Free

NET WT 2.5 OZ (71 g)